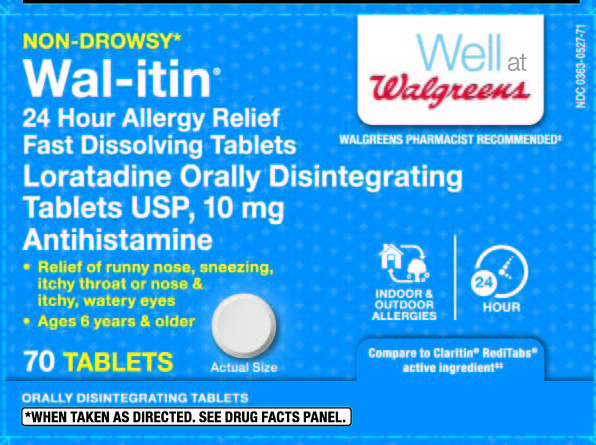 DRUG LABEL: Loratadine
NDC: 0363-0527 | Form: TABLET, ORALLY DISINTEGRATING
Manufacturer: Walgreen Company
Category: otc | Type: HUMAN OTC DRUG LABEL
Date: 20150331

ACTIVE INGREDIENTS: LORATADINE 10 mg/1 1
INACTIVE INGREDIENTS: ASPARTAME; CROSCARMELLOSE SODIUM; MAGNESIUM STEARATE; MANNITOL; SODIUM STEARYL FUMARATE

Drug Facts

ACTIVE INGREDIENT (IN EACH TABLET)

Loratadine USP, 10 mg

PURPOSE

Antihistamine

USES

Temporarily relieves these symptoms due to hay fever or other upper respiratory allergies:

- runny nose
- itchy, watery eyes
- sneezing
- itching of the nose or throat

WARNINGS

Do not use

If you have ever had an allergic reaction to this product or any of its ingredients.

Ask a doctor before use if you have

Liver or kidney disease. Your doctor should determine if you need a different dose.

When using this product

Do not take more than directed. Taking more than directed may cause drowsiness.

Stop use and ask a doctor if

An allergic reaction to this product occurs. Seek medical help right away.

If pregnant or breast-feeding

Ask a health professional before use.

Keep out of reach of children.

In case of overdose, get medical help or contact a Poison Control Center right away (1-800-222-1222).

DIRECTIONS

- place 1 tablet on tongue; tablet disintegrates, with or without water

adults and children 6 years and over | 1 tablet daily; not more than 1 tablet in 24 hours
children under 6 years of age | ask a doctor
consumers with liver or kidney disease | ask a doctor

OTHER INFORMATION

- Phenylketonurics: Contains Phenylalanine 0.6 mg Per Tablet.
- TAMPER EVIDENT: DO NOT USE IF BLISTER UNITS ARE TORN, BROKEN OR SHOW ANY SIGNS OF TAMPERING.
- store between 20° to 25° C (68° to 77° F). Protect from excessive moisture.
- use tablet immediately after opening individual blister.

INACTIVE INGREDIENTS

Aspartame, croscarmellose sodium, magnesium stearate, mannitol, mint flavor, sodium stearyl fumarate, strawberry cream flavor, tutti-frutti flavor

QUESTIONS?

Call 1-800-406-7984

PRINCIPAL DISPLAY PANEL

NON-DROWSY*

Well at Walgreens

NDC 0363-0527-71

Wal-itin®

WALGREENS PHARMACIST RECOMMENDED‡

24 Hour Allergy Relief

Fast Dissolving Tablets

Loratadine Orally Disintegrating Tablets USP, 10 mg

Antihistamine

- Relief of runny nose, sneezing, Itchy throat or nose & Itchy, watery eyes
- Ages 6 years & older

70 TABLETS

INDOOR/OUTDOOR ALLERGIES

24 HOUR

Compare to Claritin® RediTabs® active ingredient‡‡

ORALLY DISINTEGRATING TABLETS

* When taken as directed.

See Drug Facts Panel.

DISTRIBUTED BY: WALGREEN CO.

200 WILMOT RD., DEERFIELD, IL 60015

5115100/ORG0315-F